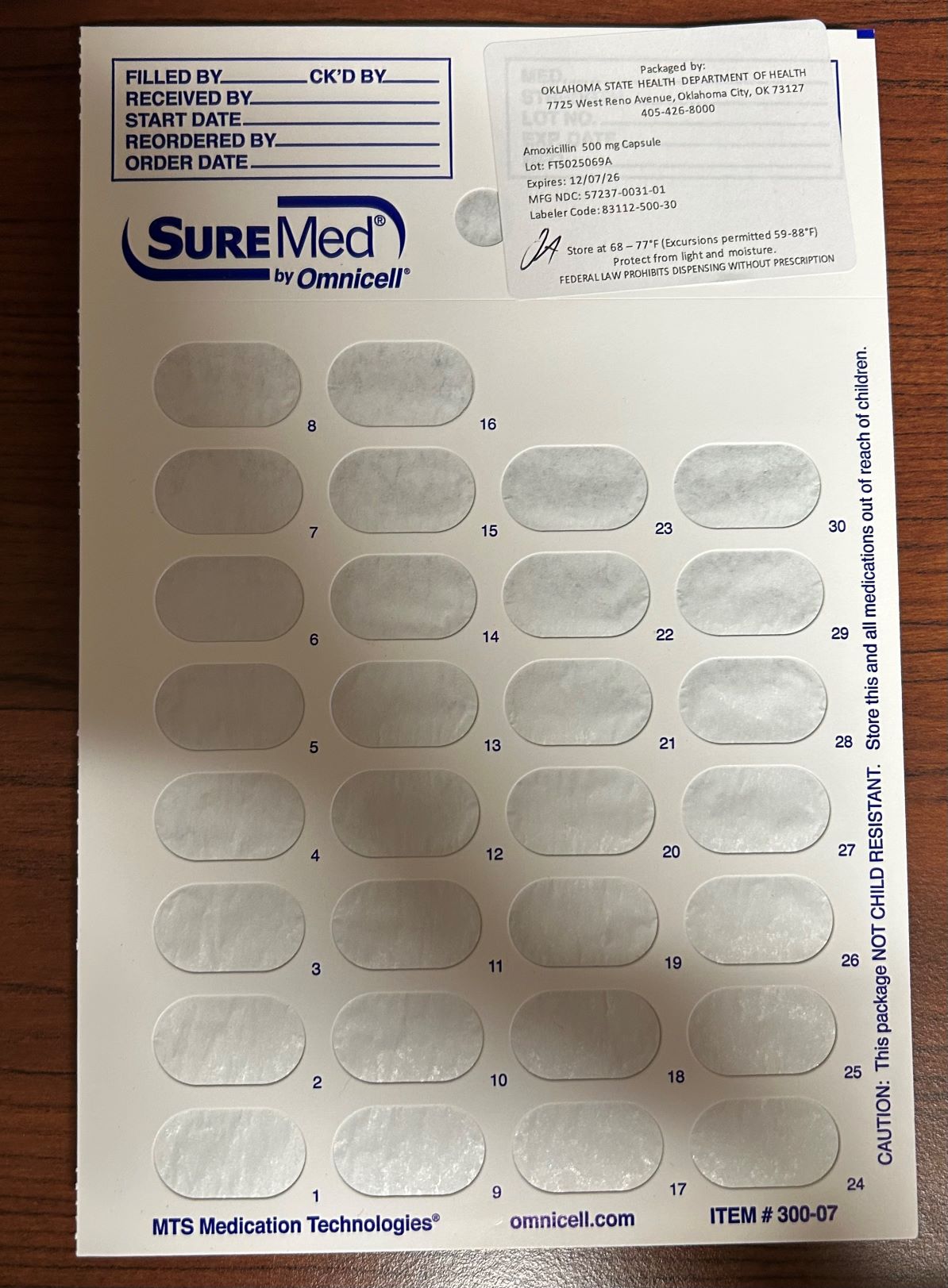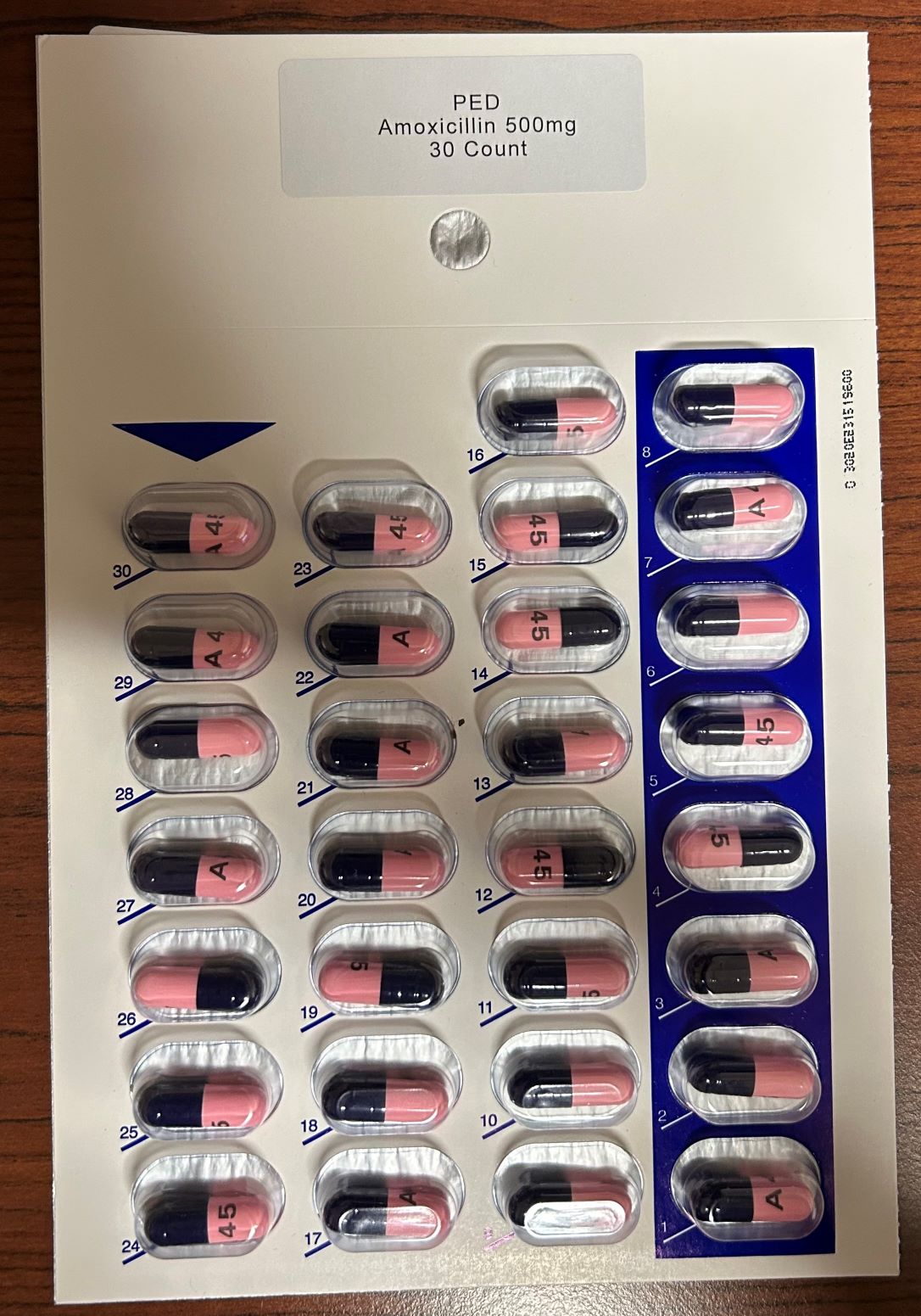 DRUG LABEL: Amoxicillin 500 mg
NDC: 83112-500 | Form: CAPSULE
Manufacturer: Health Department, Oklahoma State
Category: prescription | Type: HUMAN PRESCRIPTION DRUG LABEL
Date: 20251213

ACTIVE INGREDIENTS: AMOXICILLIN 500 mg/1 1

Amoxicillin 500 mg Pack

Precaustions from Manufacturer Package Insert

5.1 Anaphylactic Reactions

Serious and occasionally fatal hypersensitivity (anaphylactic) reactions have been reported in patients on penicillin therapy including amoxicillin. Although anaphylaxis is more frequent following parenteral therapy, it has occurred in patients on oral penicillins. These reactions are more likely to occur in individuals with a history of penicillin hypersensitivity and/or a history of sensitivity to multiple allergens. There have been reports of individuals with a history of penicillin hypersensitivity who have experienced severe reactions when treated with cephalosporins. Before initiating therapy with amoxicillin, careful inquiry should be made regarding previous hypersensitivity reactions to penicillins, cephalosporins, or other allergens. If an allergic reaction occurs, amoxicillin should be discontinued and appropriate therapy instituted.

5.2 Clostridium difficile Associated Diarrhea

Clostridium difficile associated diarrhea (CDAD) has been reported with use of nearly all antibacterial agents, including amoxicillin, and may range in severity from mild diarrhea to fatal colitis. Treatment with antibacterial agents alters the normal flora of the colon leading to overgrowth of C. difficile.
C. difficile produces toxins A and B which contribute to the development of CDAD. Hypertoxin-producing strains of C. difficile cause increased morbidity and mortality, as these infections can be refractory to antimicrobial therapy and may require colectomy. CDAD must be considered in all patients who present with diarrhea following antibacterial use. Careful medical history is necessary since CDAD has been reported to occur over 2 months after the administration of antibacterial agents.
If CDAD is suspected or confirmed, ongoing antibiotic use not directed against C. difficile may need to be discontinued. Appropriate fluid and electrolyte management, protein supplementation, antibiotic treatment of C. difficile, and surgical evaluation should be instituted as clinically indicated.

5.3 Development of Drug-Resistant Bacteria

Prescribing amoxicillin in the absence of a proven or strongly suspected bacterial infection is unlikely to provide benefit to the patient and increases the risk of the development of drug-resistant bacteria.

5.4 Use in Patients With Mononucleosis

A high percentage of patients with mononucleosis who receive amoxicillin develop an erythematous skin rash. Thus amoxicillin should not be administered to patients with mononucleosis.